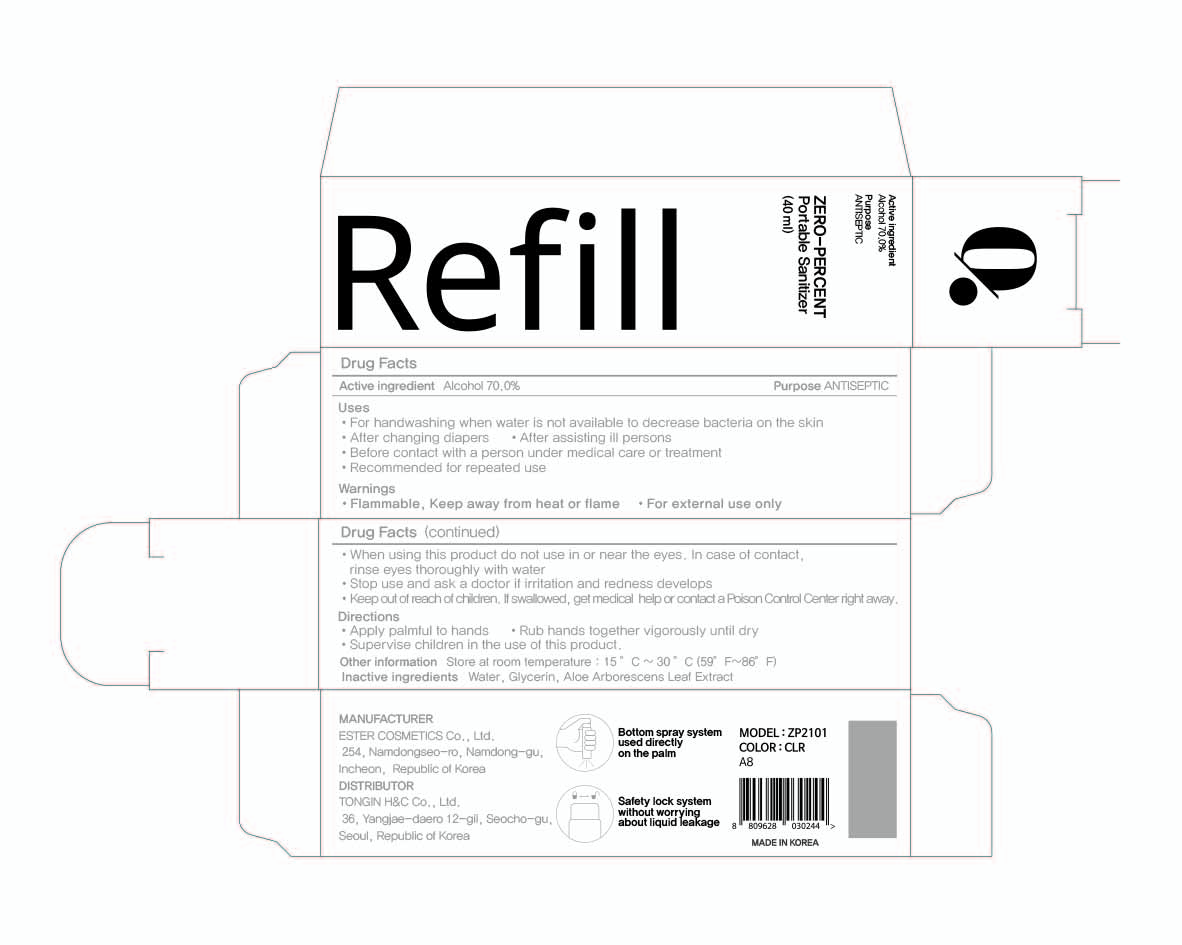 DRUG LABEL: ZERO-PERCENT Portable Sanitizer Refill
NDC: 74004-044 | Form: LIQUID
Manufacturer: Ester Co., Ltd.
Category: otc | Type: HUMAN OTC DRUG LABEL
Date: 20201006

ACTIVE INGREDIENTS: ALCOHOL 28 mL/40 mL
INACTIVE INGREDIENTS: GLYCERIN; ALOE ARBORESCENS LEAF; WATER

[4] ZERO-PERCENT Portable Sanitizer Refill (Fragrance-free)
74004-044-02
Box